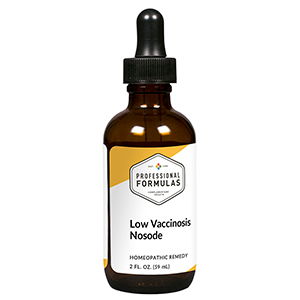 DRUG LABEL: Low Vaccinosis Nosode
NDC: 63083-4024 | Form: LIQUID
Manufacturer: Professional Complementary Health Formulas
Category: homeopathic | Type: HUMAN OTC DRUG LABEL
Date: 20190815

ACTIVE INGREDIENTS: OYSTER SHELL CALCIUM CARBONATE, CRUDE 6 [hp_X]/59 mL; SILICON DIOXIDE 6 [hp_X]/59 mL; THUJA OCCIDENTALIS LEAF 6 [hp_X]/59 mL; LAURTRIMONIUM BROMIDE 9 [hp_X]/59 mL; MUMPS VIRUS 9 [hp_X]/59 mL; CLOSTRIDIUM TETANI TOXOID ANTIGEN (FORMALDEHYDE INACTIVATED) 9 [hp_X]/59 mL; ANGUILLA ROSTRATA BLOOD SERUM 12 [hp_X]/59 mL; SERUM, HORSE 12 [hp_X]/59 mL
INACTIVE INGREDIENTS: ALCOHOL; WATER

N24

ACTIVE INGREDIENTS

Calcarea carbonica 6X, 30X
Silicea 6X, 30X
Thuja occidentalis 6X, 30X
DTTAB 9X
MMR 9X
Tetanus 9X
Serum anguillae 12X
Serum de yersin 12X
Serum equine 12X

QUESTIONS

Professional Formulas

PO Box 2034 Lake Oswego, OR 97035

INDICATIONS

For the temporary relief of aches, pains, or stiffness of muscles or joints, occasional headache, tiredness, or upset stomach.*

PURPOSE

*Claims based on traditional homeopathic practice, not accepted medical evidence. Not FDA evaluated.

WARNINGS

Consult a doctor if condition worsens or if symptoms persist. Keep out of the reach of children. In case of overdose, get medical help or contact a poison control center right away. If pregnant or breastfeeding, ask a healthcare professional before use.

Keep out of the reach of children.

PREGNANCY OR BREAST FEEDING

If pregnant or breastfeeding, ask a healthcare professional before use.

DIRECTIONS

Place drops under tongue 30 minutes before/after meals. Adults and children 12 years and over: Take 10 to 15 drops once weekly or monthly. If mild symptoms are present, take 10 drops up to 3 times per day. Consult a physician for use in children under 12 years of age.

OTHER INFORMATION

Tamper resistant. If seal is broken, do not use. After opening, close container tightly and store at room temperature away from heat.

INACTIVE INGREDIENTS

20% ethanol, purified water.

LABEL

Est 1985

Professional Formulas

Complementary Health

Low Vaccinosis Nosode

Homeopathic Remedy

2 FL. OZ. (59 mL)